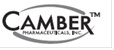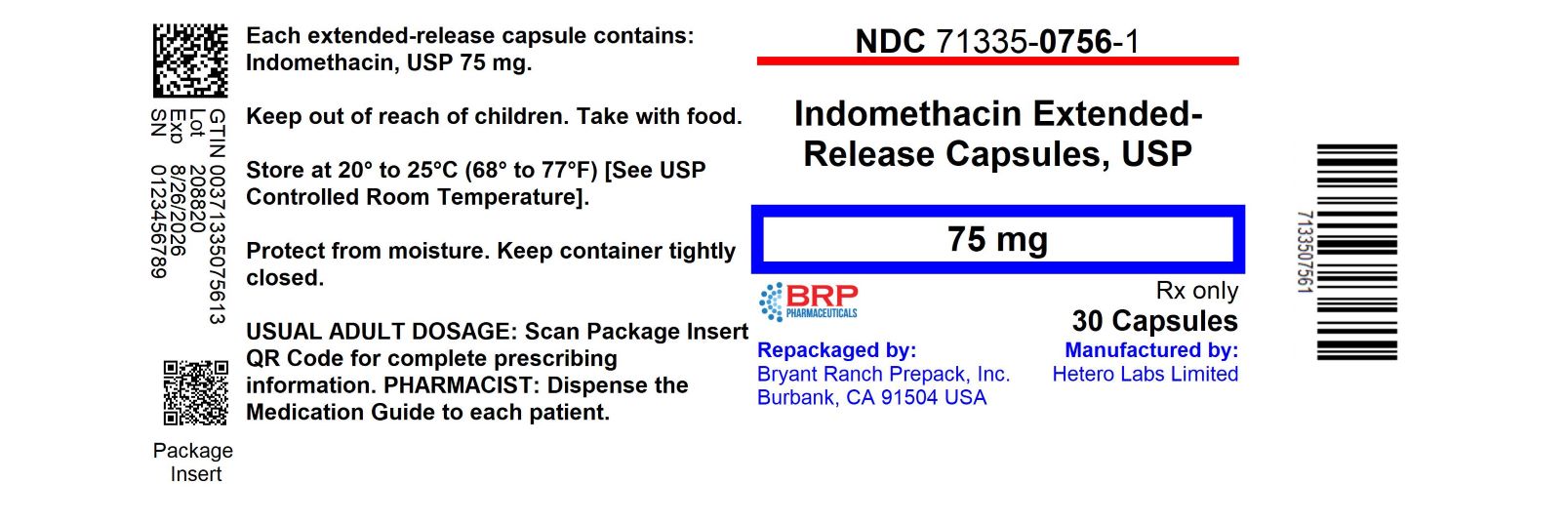 DRUG LABEL: Indomethacin
NDC: 71335-0756 | Form: CAPSULE, EXTENDED RELEASE
Manufacturer: Bryant Ranch Prepack
Category: prescription | Type: Human Prescription Drug Label
Date: 20250926

ACTIVE INGREDIENTS: INDOMETHACIN 75 mg/1 1
INACTIVE INGREDIENTS: SUCROSE; POVIDONE, UNSPECIFIED; MANNITOL; ISOPROPYL ALCOHOL; TALC; GELATIN, UNSPECIFIED; FERRIC OXIDE YELLOW; TITANIUM DIOXIDE; SODIUM LAURYL SULFATE; SHELLAC; ALCOHOL; BUTYL ALCOHOL; PROPYLENE GLYCOL; AMMONIA; FERROSOFERRIC OXIDE; POTASSIUM CATION

Indomethacin Extended Release Capsules, USP

BOXED WARNING

Cardiovascular Thrombotic Events
• Nonsteroidal anti-inflammatory drugs (NSAIDs) cause an increased risk of serious cardiovascular thrombotic events, including myocardial infarction and stroke, which can be fatal. This risk may occur early in treatment and may increase with duration of use [see Warnings and Precautions].
• Indomethacin extended-release capsules are contraindicated in the setting of coronary artery bypass graft (CABG) surgery [see Contraindications and Warnings].
Gastrointestinal Risk• NSAIDs cause an increased risk of serious gastrointestinal adverse events including bleeding, ulceration, and perforation of the stomach or intestines, which can be fatal. These events can occur at any time during use and without warning symptoms. Elderly patients are at greater risk for serious gastrointestinal events (see WARNINGS).

DESCRIPTION

Indomethacin cannot be considered a simple analgesic and should not be used in conditions other than those recommended under INDICATIONS AND USAGE.
Indomethacin is a non-steroidal anti-inflammatory indole derivative designated chemically as 1-(4-chlorobenzoyl)-5-methoxy-2-methyl-1H-indole-3-acetic acid. Indomethacin, USP is practically insoluble in water and sparingly soluble in alcohol. It has a pKa of 4.5 and is stable in neutral or slightly acidic media and decomposes in strong alkali.
The structural formula is:

C19H16ClNO4 M.W. 357.80
Each extended-release capsule, for oral administration contains 75 mg of indomethacin and the following inactive ingredients: sugar spheres, povidone, mannitol, isopropyl alcohol, talc. The hard gelatin shell consists of gelatin, iron oxide yellow, titanium dioxide, sodium lauryl sulfate.
The imprinting ink contains the following: shellac, dehydrated alcohol, isopropyl alcohol, butyl alcohol, propylene glycol, strong ammonia solution, black iron oxide E172 dye and potassium hydroxide.
This product meets USP Drug Release Test 2 Specifications.

CLINICAL PHARMACOLOGY

Indomethacin is a nonsteroidal drug with anti-inflammatory, antipyretic and analgesic properties. Its mode of action, like that of other anti-inflammatory drugs, is not known. However, its therapeutic action is not due to pituitary-adrenal stimulation.

Indomethacin is a potent inhibitor of prostaglandin synthesis in vitro. Concentrations are reached during therapy which have been demonstrated to have an effect in vivo as well. Prostaglandins sensitize afferent nerves and potentiate the action of bradykinin in inducing pain in animal models. Moreover, prostaglandins are known to be among the mediators of inflammation. Since indomethacin is an inhibitor of prostaglandin synthesis, its mode of action may be due to a decrease of prostaglandins in peripheral tissues.

Indomethacin has been shown to be an effective anti-inflammatory agent, appropriate for long-term use in rheumatoid arthritis, ankylosing spondylitis, and osteoarthritis.

Indomethacin affords relief of symptoms; it does not alter the progressive course of the underlying disease.

Indomethacin suppresses inflammation in rheumatoid arthritis as demonstrated by relief of pain and reduction of fever, swelling and tenderness. Improvement in patients treated with indomethacin for rheumatoid arthritis has been demonstrated by a reduction in joint swelling, average number of joints involved and morning stiffness; by increased mobility as demonstrated by a decrease in walking time; and by improved functional capability as demonstrated by an increase in grip strength.

Indomethacin has been reported to diminish basal and CO2 stimulated cerebral blood flow in healthy volunteers following acute oral and intravenous administration. In one study, after one week of treatment with orally administered indomethacin, this effect on basal cerebral blood flow had disappeared. The clinical significance of this effect has not been established.

Indomethacin extended-release capsules (75 mg) are designed to release 25 mg of drug initially and the remaining 50 mg over approximately 12 hours (90% of dose absorbed by 12 hours). Plasma concentrations of indomethacin fluctuate less and are more sustained following administration of indomethacin extended-release capsules than following administration of 25 mg indomethacin capsules given at 4 to 6 hour intervals. In multiple-dose comparisons, the mean daily steady state plasma level of indomethacin attained with daily administration of indomethacin extended-release capsules 75 mg was indistinguishable from that following indomethacin 25 mg capsules given at 0, 6 and 12 hours daily. However, there was a significant difference in indomethacin plasma levels between the two dosage regimens especially after 12 hours.
Controlled clinical studies of safety and efficacy in patients with osteoarthritis have shown that one capsule of indomethacin extended-release was clinically comparable to one 25 mg indomethacin capsule t.i.d.; and in controlled clinical studies in patients with rheumatoid arthritis, one capsule of indomethacin extended-release taken in the morning and one in the evening were clinically indistinguishable from one 50 mg capsule of indomethacin t.i.d.
Indomethacin is eliminated via renal excretion, metabolism and biliary excretion. Indomethacin undergoes appreciable enterohepatic circulation. The mean half-life of indomethacin is estimated to be about 4.5 hours. With a typical therapeutic regimen of 25 or 50 mg t.i.d., the steady state plasma concentrations of indomethacin are an average 1.4 times those following the first dose.
Indomethacin exists in the plasma as the parent drug and its desmethyl, desbenzoyl and desmethyldesbenzoyl metabolites, all in the unconjugated form. About 60 percent of an oral dosage is recovered in urine as drug and metabolites (26 percent as indomethacin and its glucuronide) and 33 percent is recovered in feces (1.5 percent as indomethacin).
About 99% of indomethacin is bound to protein in plasma over the expected range of therapeutic plasma concentrations. Indomethacin has been found to cross the blood-brain barrier and the placenta.

INDICATIONS & USAGE

Carefully consider the potential benefits and risks of indomethacin extended-release capsules and other treatment options before deciding to use indomethacin extended-release capsules. Use the lowest effective dose for the shortest duration consistent with individual patient treatment goals (see WARNINGS).

Indomethacin extended-release capsules have been found effective in active stages of the following:

1. Moderate to severe rheumatoid arthritis including acute flares of chronic disease.
2. Moderate to severe ankylosing spondylitis.
3. Moderate to severe osteoarthritis.
4. Acute painful shoulder (bursitis and/or tendinitis).
Indomethacin extended-release capsules, USP are not recommended for the treatment of acute gouty arthritis.
Indomethacin may enable the reduction of steroid dosage in patients receiving steroids for the more severe forms of rheumatoid arthritis. In such instances the steroid dosage should be reduced slowly and the patients followed very closely for any possible adverse effects.
The use of indomethacin in conjunction with aspirin or other salicylates is not recommended. Controlled clinical studies have shown that the combined use of indomethacin and aspirin does not produce any greater therapeutic effect than the use of indomethacin alone. Furthermore, in one of these clinical studies, the incidence of gastrointestinal side effects was significantly increased with combined therapy. (See PRECAUTIONS,Drug Interactions).

CONTRAINDICATIONS

Indomethacin extended-release capsules are contraindicated in patients with known hypersensitivity to indomethacin.
Indomethacin extended-release capsules should not be given to patients who have experienced asthma, urticaria, or allergic-type reactions after taking aspirin or other NSAIDs. Severe, rarely fatal, anaphylactic-like reactions to NSAIDs have been reported in such patients (see WARNINGS: Anaphylactoid Reactions, and Precautions: Preexisting Asthma).
Indomethacin extended-release capsules is contraindicated for the treatment of perioperative pain in the setting of coronary artery bypass graft (CABG) surgery (see WARNINGS).

WARNINGS

Cardiovascular Effects

Cardiovascular Thrombotic Events
Clinical trials of several COX-2 selective and nonselective NSAIDs of up to three years duration have shown an increased risk of serious cardiovascular (CV) thrombotic events, including myocardial infarction (MI) and stroke, which can be fatal. Based on available data, it is unclear that the risk for CV thrombotic events is similar for all NSAIDs. The relative increase in serious CV thrombotic events over baseline conferred by NSAID use appears to be similar in those with and without known CV disease or risk factors for CV disease. However, patients with known CV disease or risk factors had a higher absolute incidence of excess serious CV thrombotic events, due to their increased baseline rate. Some observational studies found that this increased risk of serious CV thrombotic events began as early as the first weeks of treatment. The increase in CV thrombotic risk has been observed most consistently at higher doses.
To minimize the potential risk for an adverse CV event in NSAID-treated patients, use the lowest effective dose for the shortest duration possible. Physicians and patients should remain alert for the development of such events, throughout the entire treatment course, even in the absence of previous CV symptoms. Patients should be informed about the symptoms of serious CV events and the steps to take if they occur.
There is no consistent evidence that concurrent use of aspirin mitigates the increased risk of serious CV thrombotic events associated with NSAID use. The concurrent use of aspirin and an NSAID, such as indomethacin, increases the risk of serious gastrointestinal (GI) events [see Warnings].
Status Post Coronary Artery Bypass Graft (CABG) Surgery
Two large, controlled clinical trials of a COX-2 selective NSAID for the treatment of pain in the first 10 to 14 days following CABG surgery found an increased incidence of myocardial infarction and stroke. NSAIDs are contraindicated in the setting of CABG [see Contraindications].
Post-MI Patients
Observational studies conducted in the Danish National Registry have demonstrated that patients treated with NSAIDs in the post-MI period were at increased risk of reinfarction, CV-related death, and all-cause mortality beginning in the first week of treatment. In this same cohort, the incidence of death in the first year post MI was 20 per 100 person years in NSAID-treated patients compared to 12 per 100 person years in non-NSAID exposed patients. Although the absolute rate of death declined somewhat after the first year post-MI, the increased relative risk of death in NSAID users persisted over at least the next four years of follow-up.
Avoid the use of indomethacin extended-release capsules in patients with a recent MI unless the benefits are expected to outweigh the risk of recurrent CV thrombotic events. If indomethacin extended-release capsules are used in patients with a recent MI, monitor patients for signs of cardiac ischemia.
Hypertension
NSAIDs, including indomethacin extended-release capsules, can lead to onset of new hypertension or worsening of preexisting hypertension, either of which may contribute to the increased incidence of CV events. Patients taking thiazides or loop diuretics may have impaired response to these therapies when taking NSAIDs. NSAIDs, including indomethacin extended-release capsules, should be used with caution in patients with hypertension. Blood pressure (BP) should be monitored closely during the initiation of NSAID treatment and throughout the course of therapy.
Heart Failure and Edema
The Coxib and traditional NSAID Trialists’ Collaboration meta-analysis of randomized controlled trials demonstrated an approximately two-fold increase in hospitalizations for heart failure in COX-2 selective-treated patients and nonselective NSAID-treated patients compared to placebo-treated patients. In a Danish National Registry study of patients with heart failure, NSAID use increased the risk of MI, hospitalization for heart failure, and death.
Additionally, fluid retention and edema have been observed in some patients treated with NSAIDs. Use of indomethacin may blunt the CV effects of several therapeutic agents used to treat these medical conditions [e.g., diuretics, ACE inhibitors, or angiotensin receptor blockers (ARBs)] [see Drug Interactions].
Avoid the use of indomethacin extended-release capsules in patients with severe heart failure unless the benefits are expected to outweigh the risk of worsening heart failure. If indomethacin extended-release capsules are used in patients with severe heart failure, monitor patients for signs of worsening heart failure.

Gastrointestinal Effects

Risk of Ulceration,Bleeding and Perforation

NSAIDs, including indomethacin extended-release capsules, can cause serious gastrointestinal (GI) adverse events including inflammation, bleeding, ulceration, and perforation of the stomach, small intestine, or large intestine, which can be fatal. These serious adverse events can occur at any time, with or without warning symptoms, in patients treated with NSAIDs. Only one in five patients, who develop a serious upper GI adverse event on NSAID therapy is symptomatic. Upper GI ulcers, gross bleeding, or perforation caused by NSAIDs occur in approximately 1% of patients treated for 3 to 6 months, and in about 2 to 4% of patients treated for one year. These trends continue with longer duration of use, increasing the likelihood of developing a serious GI event at some time during the course of therapy. However, even short-term therapy is not without risk.
NSAIDs should be prescribed with extreme caution in those with a prior history of ulcer disease or gastrointestinal bleeding. Patients with a prior history of peptic ulcer disease and/or gastrointestinal bleeding who use NSAIDs have a greater than 10-fold increased risk for developing a GI bleed compared to patients with neither of these risk factors. Other factors that increase the risk for GI bleeding in patients treated with NSAIDs include concomitant use of oral corticosteroids or anticoagulants, longer duration of NSAID therapy, smoking, use of alcohol, older age, and poor general health status.
Most spontaneous reports of fatal GI events are in elderly or debilitated patients and therefore, special care should be taken in treating this population.
To minimize the potential risk for an adverse GI event in patients treated with an NSAID, the lowest effective dose should be used for the shortest possible duration. Patients and physicians should remain alert for signs and symptoms of GI ulceration and bleeding during NSAID therapy and promptly initiate additional evaluation and treatment if a serious GI adverse event is suspected. This should include discontinuation of the NSAID until a serious GI adverse event is ruled out. For high risk patients, alternate therapies that do not involve NSAIDs should be considered.

Renal Effects

Long-term administration of NSAIDs has resulted in renal papillary necrosis and other renal injury. Renal toxicity has also been seen in patients in whom renal prostaglandins have a compensatory role in the maintenance of renal perfusion. In these patients, administration of a nonsteroidal anti-inflammatory drug may cause a dose-dependent reduction in prostaglandin formation and, secondarily, in renal blood flow, which may precipitate over renal decompensation. Patients at greatest risk of this reaction are those with impaired renal function, heart failure, liver dysfunction, those taking diuretics and ACE inhibitors, and the elderly. Discontinuation of NSAID therapy is usually followed by recovery to the pretreatment state.
Advanced Renal Disease
No information is available from controlled clinical studies regarding the use of indomethacin extended-release capsules in patients with advanced renal disease. Therefore, treatment with indomethacin extended-release capsules is not recommended in these patients with advanced renal disease. If indomethacin extended-release capsules therapy must be initiated, close monitoring of the patient's renal function is advisable.

Anaphylactoid Reactions

As with other NSAIDs, anaphylactoid reactions may occur in patients without known prior exposure to indomethacin extended-release capsules. Indomethacin extended-release capsules should not be given to patients with the aspirin triad. This symptom complex typically occurs in asthmatic patients who experience rhinitis with or without nasal polyps, or who exhibit severe, potentially fatal bronchospasm after taking aspirin or other NSAIDs (see CONTRAINDICATIONS and PRECAUTIONS::(PreexistingAsthma).Emergency help should be sought in cases where an anaphylactoid reaction occurs.

Skin Reactions

NSAIDs, including indomethacin extended-release capsules, can cause serious skin adverse events such as exfoliative dermatitis, Stevens-Johnson Syndrome (SJS), and toxic epidermal necrolysis (TEN), which can be fatal. These serious events may occur without warning. Patients should be informed about the signs and symptoms of serious skin manifestations and use of the drug should be discontinued at the first appearance of skin rash or any other sign of hypersensitivity.

Pregnancy

In late pregnancy, as with other NSAIDs, indomethacin extended-release capsules should be avoided because it may cause premature closure of the ductus arteriosus.

PRECAUTIONS

General Precautions

Indomethacin extended-release capsules cannot be expected to substitute for corticosteroids or to treat corticosteroid insufficiency. Abrupt discontinuation of corticosteroids may lead to disease exacerbation. Patients on prolonged corticosteroid therapy should have their therapy tapered slowly if a decision is made to discontinue corticosteroids.

The pharmacological activity of indomethacin extended-release capsules in reducing fever and inflammation may diminish the utility of these diagnostic signs in detecting complications of presumed noninfectious, painful conditions.

Hepatic Effects

Borderline elevations of one or more liver tests may occur in up to 15% of patients taking NSAIDs, including indomethacin extended-release capsules. These laboratory abnormalities may progress, may remain unchanged, or may be transient with continuing therapy. Notable elevations of ALT or AST (approximately three or more times the upper limit of normal) have been reported in approximately 1% of patients in clinical trials with NSAIDs. In addition, rare cases of severe hepatic reactions, including jaundice and fatal fulminant hepatitis, liver necrosis and hepatic failure, some of them with fatal outcomes have been reported.

A patient with symptoms and/or signs suggesting liver dysfunction, or in whom an abnormal liver test values has occured, should be evaluated for evidence of the development of a more severe hepatic reaction while on therapy with indomethacin extended-release capsules. If clinical signs and symptoms consistent with liver disease develop, or if systemic manifestations occur (e.g., eosinophilia, rash, etc.), indomethacin extended-release capsules should be discontinued.

Hematological Effects

Anemia is sometimes seen in patients receiving NSAIDs, including indomethacin extended-release capsules. This may be due to fluid retention, occult or gross GI blood loss, or an incompletely described effect upon erythropoiesis. Patients on long-term treatment with NSAIDs, including indomethacin extended-release capsules, should have their hemoglobin or hematocrit checked if they exhibit any signs or symptoms of anemia.
NSAIDs inhibit platelet aggregation and have been shown to prolong bleeding time in some patients. Unlike aspirin, their effect on platelet function is quantitatively less, of shorter duration, and reversible. Patients receiving indomethacin extended-release capsules who may be adversely affected by alterations in platelet function, such as those with coagulation disorders or patients receiving anticoagulants, should be carefully monitored.

Preexisting Asthma

Patients with asthma may have aspirin-sensitive asthma. The use of aspirin in patients with aspirin-sensitive asthma has been associated with severe bronchospasm which can be fatal. Since cross-reactivity, including bronchospasm, between aspirin and other non-steroidal anti-inflammatory drugs has been reported in such aspirin-sensitive patients, indomethacin extended-release capsules should not be administered to patients with this form of aspirin sensitivity and should be used with caution in patients with preexisting asthma.

Information for Patients

Patients should be informed of the following information before initiating therapy with a NSAID and periodically during the course of ongoing therapy. Patients should also be encouraged to read the NSAID Medication Guide that accompanies each prescription dispensed.

1. Cardiovascular Thrombotic Events
Advise patients to be alert for the symptoms of cardiovascular thrombotic events, including chest pain, shortness of breath, weakness, or slurring of speech, and to report any of these symptoms to their health care provider immediately [see Warnings].
2. Indomethacin extended-release capsules, like other NSAIDs, can cause GI discomfort and, rarely, serious GI side effects, such as ulcers and bleeding, which may result in hospitalization and even death. Although serious GI tract ulcerations and bleeding can occur without warning symptoms, patients should be alert for the signs and symptoms of ulcerations and bleeding, and should ask for medical advice when observing any indicative signs or symptoms including epigastric pain, dyspepsia, melena, and hematemesis. Patients should be apprised of the importance of this follow-up (see WARNINGS, Gastrointestinal Effects, Risk of Ulceration, Bleeding, and Perforation).
3. Indomethacin extended-release capsules, like other NSAIDs, can cause serious skin side effects such as exfoliative dermatitis, SJS, and TEN, which may result in hospitalization and even death. Although serious skin reactions may occur without warning, patients should be alert for the signs and symptoms of skin rash and blisters, fever, or other signs of hypersensitivity such as itching, and should ask for medical advice when observing any indicative signs or symptoms. Patients should be advised to stop the drug immediately if they develop any type of rash and contact their physicians as soon as possible.
4. Heart Failure And Edema
Advise patients to be alert for the symptoms of congestive heart failure including shortness of breath, unexplained weight gain, or edema and to contact their healthcare provider if such symptoms occur [see Warnings].
5. Patients should be informed of the warning signs and symptoms of hepatotoxicity (e.g., nausea, fatigue, lethargy, pruritus, jaundice, right upper quadrant tenderness and "flu-like" symptoms). If these occur, patients should be instructed to stop therapy and seek immediate medical therapy.
6. Patients should be informed of the signs of an anaphylactoid reaction (e.g. difficulty breathing, swelling of the face or throat). If these occur, patients should be instructed to seek immediate emergency help (see WARNINGS).

7. In late pregnancy, as with other NSAIDs, indomethacin extended-release capsules should be avoided because it will cause premature closure of the ductus arteriosus.

Laboratory Tests

Because serious GI tract ulcerations and bleeding can occur without warning symptoms, physicians should monitor for signs or symptoms of GI bleeding. Patients on long-term treatment with NSAIDs should have their CBC and a chemistry profile checked periodically. If clinical signs and symptoms consistent with liver or renal disease develop, systemic manifestations occur (e.g., eosinophilia, rash, etc.) or if abnormal liver tests persist or worsen, indomethacin extended-release capsules should be discontinued.

Drug Interactions

ACE inhibitors
Reports suggest that NSAIDs may diminish the antihypertensive effect of ACE-inhibitors. This interaction should be given consideration in patients taking NSAIDs concomitantly with ACE-inhibitors.
Aspirin
When indomethacin extended-release capsules are administered with aspirin, its protein binding is reduced, although the clearance of free indomethacin extended-release capsules is not altered. The clinical significance of this interaction is not known; however, as with other NSAIDs, concomitant administration of indomethacin and aspirin is not generally recommended because of the potential of increased adverse effects.
Furosemide
Clinical studies, as well as post marketing observations, have shown that indomethacin extended-release capsules can reduce the natriuretic effect-of furosemide and thiazides in some patients. This response has been attributed to inhibition of renal prostaglandin synthesis. During concomitant therapy with NSAIDs, the patient should be observed closely for signs of renal failure (see WARNINGS, Renal Effects), as well as to assure diuretic efficacy.
Lithium
NSAIDs have produced an elevation of plasma lithium levels and a reduction in renal lithium clearance. The mean minimum lithium concentration increased 15% and the renal clearance was decreased by approximately 20%. These effects have been attributed to inhibition of renal prostaglandin synthesis by the NSAID. Thus, when NSAIDs and lithium are administered concurrently, subjects should be carefully observed for signs of lithium toxicity.
Methotrexate
NSAIDs have been reported to competitively inhibit methotrexate accumulation in rabbit kidney slices. This may indicate that they could enhance the toxicity of methotrexate. Caution should be used when NSAIDs are administered concomitantly with methotrexate.
Warfarin
The effects of warfarin and NSAIDs on GI bleeding are synergistic, such that users of both drugs together have a risk of serious GI bleeding higher than users of either drug alone.

Drug & OR Laboratory Test Interactions

Only if positive interactions have been observed. (See 201.57 (f)(4)(N))

Carcinogenesis & Mutagenesis & Impairment Of Fertility

Usually only if significant findings have been observed. (See 201.57 (f)(5))

Pregnancy

Pregnancy Teratogenic Effects. Pregnancy Category C
Reproductive studies conducted in rats and rabbits have not demonstrated evidence of developmental abnormalities. However, animal reproduction studies are not always predictive of human response. There are no adequate and well-controlled studies in pregnant women.
Nonteratogenic Effects
Because of the known effects of nonsteroidal anti-inflammatory drugs on the fetal cardiovascular system (closure of ductus arteriosus), use during pregnancy (particularly late pregnancy) should be avoided.

Labor & Delivery

In rat studies with NSAIDs, as with other drugs known to inhibit prostaglandin synthesis, an increased incidence of dystocia, delayed parturition and decreased pup survival occurred. The effects of indomethacin extended-release capsules on labor and delivery in pregnant women are unknown.

Nursing Mothers

It is not known whether this drug is excreted in human milk. Because many drugs are excreted in human-milk and because of the potential for serious adverse reactions in nursing infants from indomethacin extended-release capsules, a decision should be made whether to discontinue nursing or to discontinue the drug, taking into account the importance of the drug to the mother.

Pediatric Use

Safety and effectiveness in pediatric patients below the age of 14 years old have not been established.

Geriatric Use

As with any NSAIDs, caution should be exercised in treating the elderly (65 years and older).

ADVERSE REACTIONS

The adverse reactions for indomethacin capsules listed in the following table have been arranged into two groups: (1) incidence greater than 1%; and (2) incidence less than 1%. The incidence for group (1) was obtained from 33 double-blind controlled clinical trials reported in the literature (1,092 patients). The incidence for group (2) was based on reports in clinical trials, in the literature, and on voluntary reports since marketing. The probability of a causal relationship exists between indomethacin and these adverse reactions, some of which have been reported only rarely.
In controlled clinical trials, the incidence of adverse reactions to indomethacin extended-release capsules and equal 24-hour doses of indomethacin capsules were similar.

Incidence greater than 1%

GASTROINTESTINAL
nausea* with or without vomiting
dyspepsia* (including indigestion, heartburn and epigastric pain)
diarrhea
abdominal distress or pain
constipation
CENTRAL NERVOUS SYSTEM
headache (11.7%)
dizziness*
vertigo
somnolence
depression and fatigue (including malaise and listlessness)
SPECIAL SENSES
tinnitus
CARDIOVASCULAR
none
METABOLIC
none
INTEGUMENTARY
none
HEMATOLOGIC
none
HYPERSENSITIVITY
none
GENITOURINARY
none
MISCELLANEOUS
none

Incidence less than 1%

GASTROINTESTINAL
anorexia
bloating (includes distention)
flatulence
peptic ulcer
gastroenteritis
rectal bleeding
proctitis
single or multiple ulcerations, including perforation and hemorrhage of the esophagus, stomach, duodenum or small and large intestines
Intestinal ulceration associated with stenosis and obstruction
gastrointestinal bleeding without obvious ulcer formation and perforation of preexisting sigmoid lesions (diverticulum, carcinoma, etc.) development of ulcerative colitis and regional ileitis
ulcerative stomatitis
toxic hepatitis and jaundice (some fatal cases have been reported)
CENTRAL NERVOUS SYSTEM
anxiety (includes nervousness)
muscle weakness
involuntary muscle movements
insomnia
muzziness
psychic disturbances including psychotic episodes
mental confusion
drowsiness
light-headedness
syncope
paresthesia
aggravation of epilepsy and parkinsonism
depersonalization
coma
peripheral neuropathy
convulsions
dysarthria
SPECIAL SENSESocular-corneal deposits and retinal disturbances, including those of the macula, have been reported in some patients on prolonged therapy with Indomethacin
blurred vision
diplopia
hearing disturbances, deafness
CARDIOVASCULAR
congestive heart failure
hypertension
hypotension
tachycardia
chest pain
arrhythmia; palpitations
METABOLIC
edema
weight gain
fluid retention
flushing or sweating
hyperglycemia
glycosuria
hyperkalemia
INTEGUMENTARY
pruritus
rash; urticaria
petechiae or ecchymosis
exfoliative dermatitis
erythema nodosum
loss of hair
Stevens-Johnson Syndrome
erythema multiforme
toxic epidermal necrolysis
HEMATOLOGIC
leukopenia
bone marrow depression
anemia secondary to obvious or occult gastrointestinal bleeding
aplastic anemia
hemolytic anemia
agranulocytosis
thrombocytopenic purpura
disseminated intravascular coagulation
HYPERSENSITIVITY
acute anaphylaxis
acute respiratory distress
rapid fall in blood pressure resembling a shock-like state
angioedema
dyspnea
asthma
purpura
angiitis
pulmonary edema
fever
GENITOURINARY
hematuria
vaginal bleeding
proteinuria, nephrotic syndrome, interstitial nephritis
BUN elevation
renal insufficiency including renal failure
MISCELLANEOUS
epistaxis
breast changes, including enlargement and tenderness, or gynecomastia

*Reactions occurring in 3% to 9% of patients treated with indomethacin. (Those reactions occurring in less than 3% of the patients are unmarked.)

Causal Relationship Unknown: Other reactions have been reported but occurred under circumstances where a causal relationship could not be established. However, in these rarely reported events, the possibility cannot be excluded. Therefore, these observations are being listed to serve as alerting information to physicians:
A rare occurrence of fulminant necrotizing fasciitis, particularly in association with Group A β-hemolytic streptococcus, has been described in persons treated with nonsteroidal anti-inflammatory agents, including indomethacin, sometimes with fatal outcome (see also PRECAUTIONS, General).
Cardiovascular: Thrombophlebitis

Hematologic: Although there have been several reports of leukemia, the supporting information is weak.

Genitourinary: Urinary frequency

OVERDOSAGE

The following symptoms may be observed following overdosage: nausea, vomiting, intense headache, dizziness, mental confusion, disorientation, or lethargy. There have been reports of paresthesias, numbness and convulsions.
Treatment is symptomatic and supportive. The stomach should be emptied as quickly as possible if the ingestion is recent. If vomiting has not occurred spontaneously, the patient should be induced to vomit with syrup of ipecac. If the patient is unable to vomit, gastric lavage should be performed. Once the stomach has been emptied, 25 g or 50 g of activated charcoal may be given. Depending on the condition of the patient, close medical observation and nursing care may be required. The patient should be followed for several days because gastrointestinal ulceration and hemorrhage have been reported as adverse reactions of indomethacin. Use of antacids may be helpful.
The oral LD50 of indomethacin in mice and rats (based on 14 day mortality response) was 50 and 12 mg/kg, respectively.

DOSAGE & ADMINISTRATION

Carefully consider the potential benefits and risks of indomethacin extended-release capsules and other treatment options before deciding to use indomethacin extended-release capsules. Use the lowest effective dose for the shortest duration consistent with individual patient treatment goals (see WARNINGS). Indomethacin extended-release capsules 75 mg are available for oral use. Indomethacin extended-release capsules can be administered once a day and can be substituted for indomethacin 25 mg capsules t.i.d. However, there will be significant differences between the two dosage regimens in indomethacin blood levels, especially after 12 hours (see CLINICAL PHARMACOLOGY). In addition, indomethacin extended-release capsules 75 mg b.i.d. can be substituted for indomethacin 50 mg capsules t.i.d. Indomethacin extended-release capsules may be substituted for all the indications of indomethacin capsules except acute gouty arthritis.
Adverse reactions appear to correlate with the size of the dose of indomethacin in most patients, but not all. Therefore, every effort should be made to determine the smallest effective dosage for the individual patient.
Always give indomethacin extended-release capsules 75 mg with food, immediately after meals or with antacids to reduce gastric irritation.
Pediatric Use: Indomethacin ordinarily should not be prescribed for children 14 years of age and under (see WARNINGS).
Adult Use: Dosage Recommendations for Active Stages of the Following:
1. Moderate to severe rheumatoid arthritis, including acute flares of chronic disease; moderate to severe ankylosing spondylitis; and moderate to severe osteoarthritis.
The following information is provided as background only and refers to immediate-release indomethacin capsules (25 mg or 50 mg):
Suggested Dosage:
The following recommendations on dosing pertain to immediate-release indomethacin capsules, and provide important information regarding the dosage and administration of indomethacin. The prescriber should be aware of this information when considering and prescribing extended-release indomethacin.
Indomethacin capsules 25 mg b.i.d. or t.i.d. If this is well tolerated, increase the daily dosage by 25 or 50 mg, if required by continuing symptoms, at weekly intervals until a satisfactory response is obtained or until a total daily dose of 150 to 200 mg is reached. DOSES ABOVE THIS AMOUNT GENERALLY DO NOT INCREASE THE EFFECTIVENESS OF THE DRUG.
In patients who have persistent night pain and/or morning stiffness, the giving of a large portion, up to a maximum of 100 mg, of the total daily dose at bedtime, either orally or by rectal suppositories, may be helpful in affording relief. The total daily dose should not exceed 200 mg. In acute flares of chronic rheumatoid arthritis, it may be necessary to increase the dosage by 25 mg or, if required, by 50 mg daily.
The following information refers to Extended-release Indomethacin Capsules (75 mg):
If indomethacin extended-release capsules are used for initiating indomethacin treatment, one capsule daily should be the usual starting dose in order to observe patient tolerance since 75 mg per day is the maximum recommended starting dose for indomethacin (see above). If indomethacin extended-release capsules are used to increase the daily dose, patients should be observed for possible signs and symptoms of intolerance since the daily increment will exceed the daily increment recommended for other dosage forms. For patients who require 150 mg of indomethacin per day and have demonstrated acceptable tolerance, indomethacin extended-release capsules 75 mg may be prescribed as one capsule twice daily.
If minor adverse effects develop as the dosage is increased, reduce the dosage rapidly to a tolerated dose and OBSERVE THE PATIENT CLOSELY.
If severe adverse reactions occur, STOP THE DRUG. After the acute phase of the disease is under control, an attempt to reduce the daily dose should be made repeatedly until the patient is receiving the smallest effective dose or the drug is discontinued.
Careful instructions to and observations of, the individual patient are essential to the prevention of serious, irreversible, including fatal, adverse reactions.
As advancing years appear to increase the possibility of adverse reactions, indomethacin extended-release capsules should be used with greater care in the aged.
2. Acute painful shoulder (bursitis and/or tendinitis). Initial Dose: 75 mg to 150 mg daily. When 150 mg is prescribed, give as one capsule twice daily.
The drug should be discontinued after the signs and symptoms of inflammation have been controlled for several days. The usual course of therapy is 7 to 14 days.

HOW SUPPLIED

Indomethacin Extended-release capsules USP 75 mg are size '2’ hard gelatin capsules, with dark yellow cap imprinted with 'H' and clear transparent body imprinted with '105' containing cream spherical pellet:

Product: 71335-0756

NDC: 71335-0756-1 30 CAPSULE, EXTENDED RELEASE in a BOTTLE

NDC: 71335-0756-2 60 CAPSULE, EXTENDED RELEASE in a BOTTLE

NDC: 71335-0756-3 14 CAPSULE, EXTENDED RELEASE in a BOTTLE

NDC: 71335-0756-4 10 CAPSULE, EXTENDED RELEASE in a BOTTLE

NDC: 71335-0756-5 7 CAPSULE, EXTENDED RELEASE in a BOTTLE

NDC: 71335-0756-6 15 CAPSULE, EXTENDED RELEASE in a BOTTLE

NDC: 71335-0756-7 20 CAPSULE, EXTENDED RELEASE in a BOTTLE

NDC: 71335-0756-8 90 CAPSULE, EXTENDED RELEASE in a BOTTLE

NDC: 71335-0756-9 100 CAPSULE, EXTENDED RELEASE in a BOTTLE

Store at 20° to 25°C (68° to 77°F) [see USP Controlled Room Temperature]. Protect from moisture

Repackaged/Relabeled by:

Bryant Ranch Prepack, Inc.
Burbank, CA 91504

SPL MEDGUIDE

Indomethacin Extended-release Capsules, USP

Medication Guide for Non steroidal Anti-inflammatory Drugs (NSAIDs)
What is the most important information I should know about medicines called Nonsteroidal Anti-inflammatory Drugs (NSAIDs)?
NSAIDs can cause serious side effects, including:
• Increased risk of heart attack or stroke that can lead to death. This risk may happen early in treatment and may increase:
o with increasing doses of NSAIDs
o with longer use of NSAIDs

Do not take NSAIDs right before or after a heart surgery called a “coronary artery bypass graft (CABG).” Avoid taking NSAIDs after a recent heart attack, unless your healthcare provider tells you to. You may have an increased risk of another heart attack if you take NSAIDs after a recent heart attack.
• Increased risk of bleeding, ulcers, and tears (perforation) of the esophagus (tube leading from the mouth to the stomach), stomach and intestines:
o anytime during use
o without warning symptoms
o that may cause death
The risk of getting an ulcer or bleeding increases with:
o past history of stomach ulcers, or stomach or intestinal bleeding with use of NSAIDs
o taking medicines called "corticosteroids", "anticoagulants", "SSRIs", or "SNRIs"
o increasing doses of NSAIDs o older age
o longer use of NSAIDs o poor health
o smoking o advanced liver disease
o drinking alcohol o bleeding problems
NSAIDs should only be used:
o exactly as prescribed
o at the lowest dose possible for your treatment
o for the shortest time needed
What are NSAIDs?
NSAIDs are used to treat pain and redness, swelling, and heat (inflammation) from medical conditions such as different types of arthritis, menstrual cramps, and other types of short-term pain.
Who should not take a NSAIDs?

Do not take an NSAIDs:
• if you had an asthma attack, hives, or other allergic reaction with aspirin or any other NSAIDs.
• right before or after heart bypass surgery.
Before taking NSAIDs, tell your healthcare provider about all of your medical conditions, including if you:
• have liver or kidney problems
• have high blood pressure
• have asthma
• are pregnant or plan to become pregnant. Talk to your healthcare provider if you are considering taking NSAIDs during pregnancy. You should not take NSAIDs after 29 weeks of pregnancy.
• are breastfeeding or plan to breast feed.

Tell your healthcare provider about all of the medicines you take, including prescription or over-the-counter medicines, vitamins or herbal supplements. NSAIDs and some other medicines can interact with each other and cause serious side effects. Do not start taking any new medicine without talking to your healthcare provider first.
What are the possible side effects of NSAIDs?
NSAIDs can cause serious side effects, including:
See “What is the most important information I should know about medicines called Nonsteroidal Anti-inflammatory Drugs (NSAIDs)?• new or worse high blood pressure
• heart failure
• liver problems including liver failure
• kidney problems including kidney failure
• low red blood cells (anemia)
• life-threatening skin reactions
• life threatening allergic reactions
• Other side effects of NSAIDs include: stomach pain, constipation, diarrhea, gas, heartburn, nausea, vomiting, and dizziness.
Get emergency help right away if you get any of the following symptoms:
• shortness of breath or trouble breathing • slurred speech
• chest pain • swelling of the face or throat
• weakness in one part or side of your body
Stop taking your NSAID and call your healthcare provider right away if you get any of the following symptoms:
• nausea • vomit blood
• more tired or weaker than usual • there is blood in your bowel movement or it is
• diarrhea black and sticky like tar
• itching • unusual weight gain
• your skin or eyes look yellow • skin rash or blisters with fever
• indigestion or stomach pain • swelling of the arms, legs, hands and feet
• flu-like symptoms
If you take too much of your NSAID, call your healthcare provider or get medical help right away.
These are not all the possible side effects of NSAIDs. For more information, ask your healthcare provider or pharmacist about NSAIDs.
Call your doctor for medical advice about side effects. You may report side effects to FDA at 1-800-FDA-1088.
Other information about NSAIDs
• Aspirin is an NSAID but it does not increase the chance of a heart attack. Aspirin can cause bleeding in the brain, stomach, and intestines. Aspirin can also cause ulcers in the stomach and intestines.

• Some NSAIDs are sold in lower doses without a prescription (over-the-counter). Talk to your healthcare provider before using over-the-counter NSAIDs for more than 10 days.
General information about the safe and effective use of NSAIDs

Medicines are sometimes prescribed for purposes other than those listed in a Medication Guide. Do not use NSAIDs for a condition for which it was not prescribed. Do not give NSAIDs to other people, even if they have the same symptoms that you have. It may harm them.
If you would like more information about NSAIDs, talk with your healthcare provider. You can ask your pharmacist or healthcare provider for information about NSAIDs that is written for health professionals.
This Medication Guide has been approved by the U.S. Food and Drug Administration.

Manufactured for:
Camber Pharmaceuticals, Inc.
Piscataway, NJ 08854
By: HETEROTM

Hetero Labs Limited
Jeedimetla, Hyderabad – 500 055, India.
Revised: August 2015